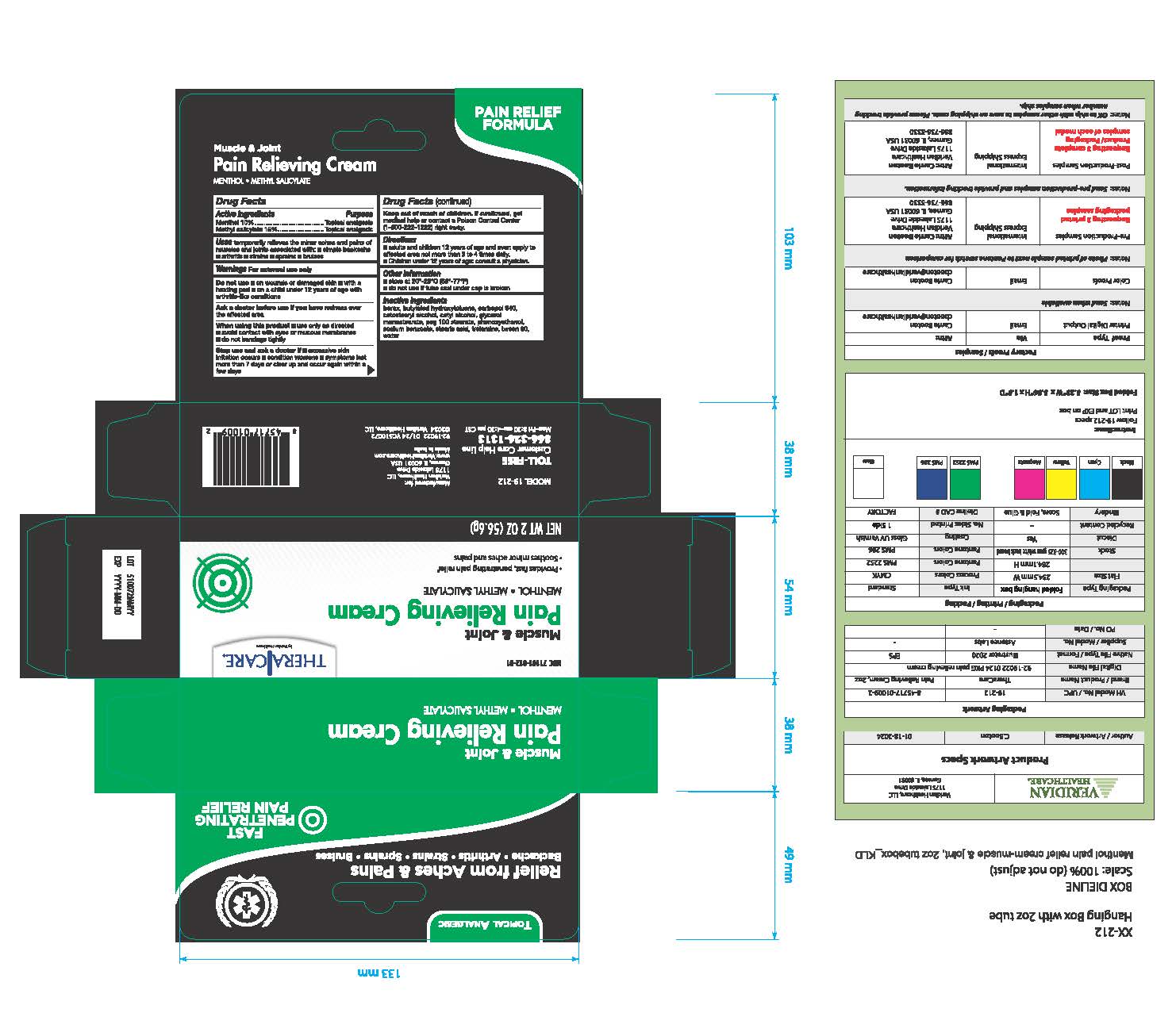 DRUG LABEL: TheraCare Muscle and Join Pain Relieving Cream
NDC: 71101-012 | Form: CREAM
Manufacturer: Veridian Healthcare
Category: otc | Type: HUMAN OTC DRUG LABEL
Date: 20260203

ACTIVE INGREDIENTS: MENTHOL, UNSPECIFIED FORM 100 mg/1 g; METHYL SALICYLATE 150 mg/1 g
INACTIVE INGREDIENTS: BUTYLATED HYDROXYTOLUENE; PHENOXYETHANOL; CARBOMER 940; CETYL ALCOHOL; PEG-100 STEARATE; GLYCERYL MONOSTEARATE; SODIUM BENZOATE; TROLAMINE; CETOSTEARYL ALCOHOL; SODIUM BORATE; STEARIC ACID; WATER; POLYSORBATE 60

TheraCare Muscle & Join Pain Relieving Cream

Drug Facts

ACTIVE INGREDIENT

Menthol 10%

Methyl salicylate 15%

Active ingredients | Purpose
Menthol 10% | Topical analgesic
Methyl salicylate 15% | Topical analgesic

Uses

temporarily relieves the minor aches and pains of muscles and joints associated with:

- simple backache
- arthritis
- strains
- bruises
- sprains

Warnings

For external use only.

Do not use

- on wounds or damaged skin
- with a heating pad
- on a child under 12 years of age with arthritis-like conditions

Ask a doctor before use if you have redness over the affected area

When using this product

- avoid contact with eyes or mucous membranes
- do not bandage tightly

Stop use and ask a doctor if

- excessive skin irritation occurs
- condition worsens
- symptoms last more than 7 days or clear up and occur again within a few days

Keep out of reach of children. If swallowed, get medical help or contact a Poison Control Center right away. (1-800-222-1222)

Directions

- adults and children 12 years of age and over: apply to affected area not more than 3 to 4 times daily
- children under 12 years of age: consult a physician.

Other information

store at 20° to 25°C (68° to 77°F)

do not use if tube seal under cap is broken

Inactive ingredients

borax, butylated hydroxy1oluene, carbopol 940, cetostearyl alcohol, cetyl alcohol, glycerol monostearate, peg 100 stearate, phenoxyethanol, sodium benzoate, stearic acid, trolamine, tween 60, water